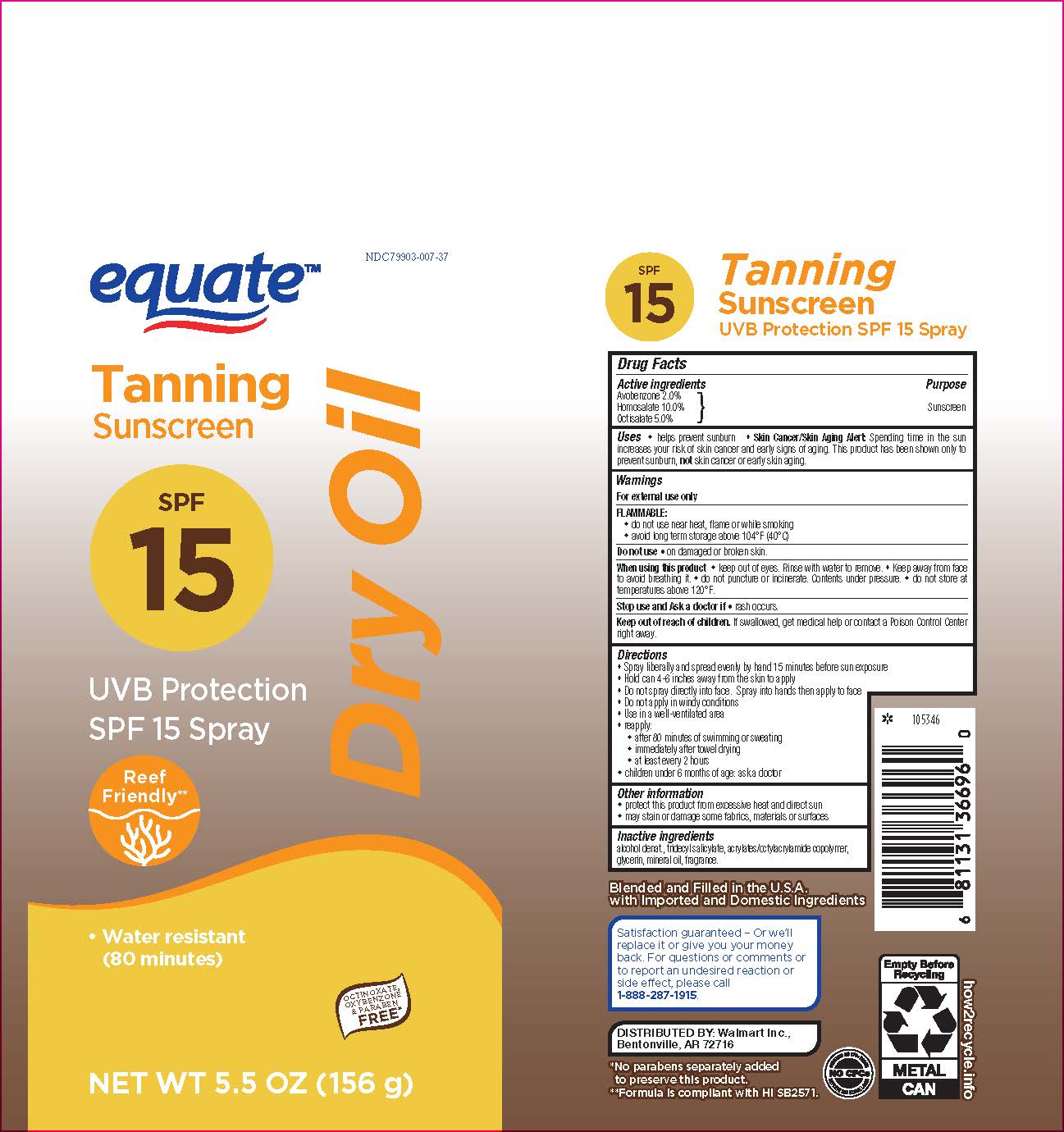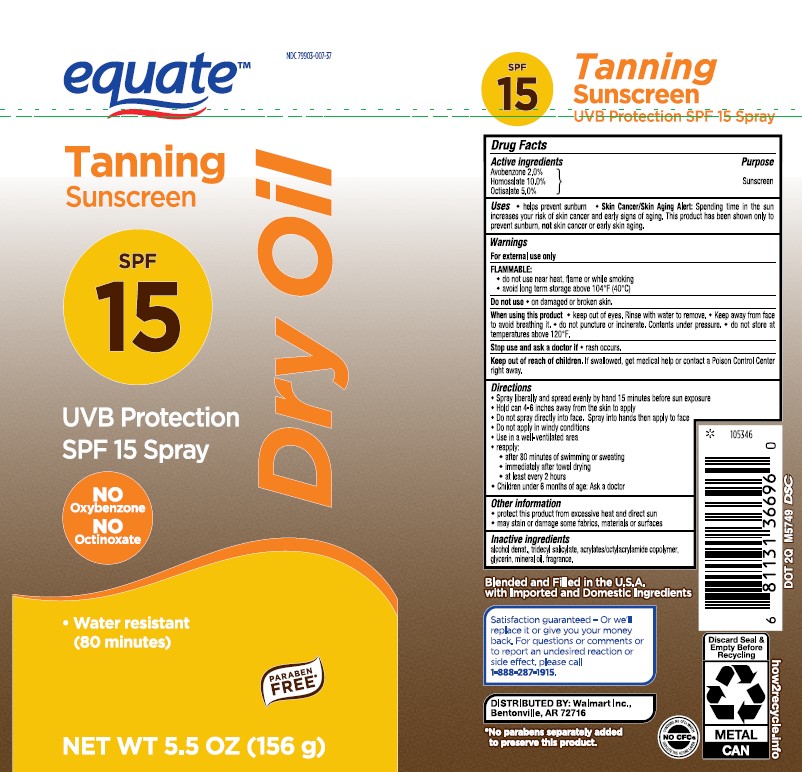 DRUG LABEL: Tanning Sunscreen UVB Protection Dry Oil
NDC: 79903-007 | Form: AEROSOL, SPRAY
Manufacturer: WAL-MART STORES INC.
Category: otc | Type: HUMAN OTC DRUG LABEL
Date: 20241023

ACTIVE INGREDIENTS: HOMOSALATE 100 mg/1 g; OCTISALATE 50 mg/1 g; AVOBENZONE 20 mg/1 g
INACTIVE INGREDIENTS: ALCOHOL; GLYCERIN; ACRYLATE/ISOBUTYL METHACRYLATE/N-TERT-OCTYLACRYLAMIDE COPOLYMER (75000 MW); LIGHT MINERAL OIL; TRIDECYL SALICYLATE

Equate Tanning Sunscreen UVB Protection SPF 15 Spray Dry Oil

Active ingredients

Avobenzone 2.0%, Homosalate 10.0%, Octisalate 5.0%

Purpose

Sunscreen

Uses

• helps prevent sunburn • Skin Cancer/Skin Aging Alert: Spending time in the sun increases your risk of skin cancer and early signs of aging. This product has been shown only to prevent sunburn, not skin cancer or early skin aging.

Warnings

For external use only

FLAMMABLE:

• do not use near heat, flame or while smoking
• avoid long term storage above 104°F (40°C)

Do not use

• on damaged or broken skin.

When using this product

• keep out of eyes. Rinse with water to remove. • Keep away from face to avoid breathing it. • do not puncture or incinerate. Contents under pressure. • do not store at temperatures above 120°F.

Stop use and Ask a doctor if

• rash occurs.

Keep out of reach of children.

If swallowed, get medical help or contact a Poison Control Center right away.

Directions

• Spray liberally and spread evenly by hand 15 minutes before sun exposure
• Hold can 4-6 inches away from the skin to apply
• Do not spray directly into face. Spray into hands then apply to face
• Do not apply in windy conditions
• Use in a well-ventilated area

• reapply:
• after 80 minutes of swimming or sweating
• immediately after towel drying
• at least every 2 hours
• children under 6 months of age: Ask a doctor

Other information

• protect the product in this container from excessive heat and direct sun
• may stain or damage some fabrics, materials or surfaces

Inactive ingredients

alcohol denat., tridecyl salicylate, acrylates/octylacrylamide copolymer, glycerin, mineral oil, fragrance.

Label

Equate Tanning Sunscreen UVB Protection SPF 15 Spray Dry Oil

5.5 oz (156 g)

NDC 79903-007-37